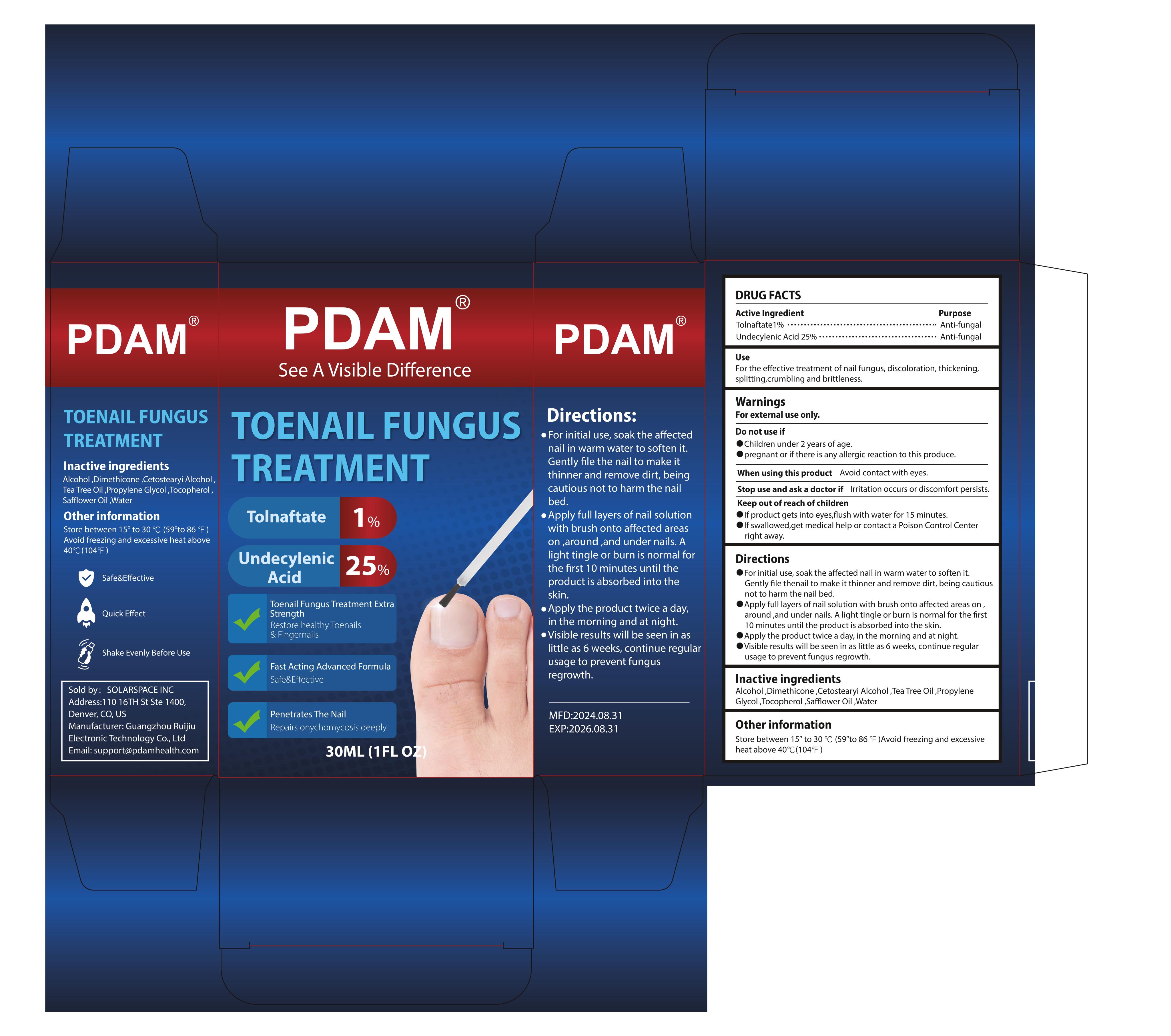 DRUG LABEL: TOENAIL FUNGUS TREATMENT  Liquid
NDC: 83767-701 | Form: LIQUID
Manufacturer: Guangzhou Ruijiu Electronic Technology Co., Ltd.
Category: otc | Type: HUMAN OTC DRUG LABEL
Date: 20240903

ACTIVE INGREDIENTS: TOLNAFTATE 1 g/100 mL; UNDECYLENIC ACID 25 g/100 mL
INACTIVE INGREDIENTS: TEA TREE OIL; CETOSTEARYL ALCOHOL; TOCOPHEROL; SAFFLOWER OIL; WATER; ALCOHOL; DIMETHICONE; PROPYLENE GLYCOL

TOENAIL FUNGUS TREATMENT Liquid

TOENAIL FUNGUS TREATMENT Liquid

ACTIVE INGREDIENT

TOLNAFTATE 1%
UNDECYLENIC ACID 25%

PURPOSE

Anti-fungal

INDICATIONS AND USAGE

For the effective treatment of nail fungus, discoloration, thickeningsplitting,crumbling and brittleness.

WARNINGS

For external use only.

DO NOT USE

Children under 2 years of age.
pregnant or if there is any allergic reaction to this produce.

When using this product Avoid contact with eyes

Stop use and ask a doctor if lrritation occurs or discomfort persists.

KEEP OUT OF REACH OF CHILDREN

If product gets into eyes,flush with water for 15 minutes.

If swallowed,get medical help or contact a Poison Control Centerright away.

DOSAGE AND ADMINISTRATION

For initial use, soak the affected nail in warm water to soften it.Gently fle thenail to make it thinner and remove dirt, being cautiousnot to harm the nail bed.
Apply full layers of nail solution with brush onto affected areas onaround ,and under nails. A light tingle or burn is normal for the frst10 minutes until the product is absorbed into the skin.
Apply the product twice a day, in the morning and at night.
Visible results will be seen in as little as 6 weeks, continue regularusage to prevent fungus regrowth.

STORAGE AND HANDLING

heat above 40'C(104°)
Store between 15° to 30 °C (59°to 86 ℉)Avoid freezing and excessive

INACTIVE INGREDIENT

ALCOHOL
DIMETHICONE
CETOSTEARYL ALCOHOL
TEA TREE OIL
PROPYLENE GLYCOL
TOCOPHEROL
SAFFLOWER OIL
WATER